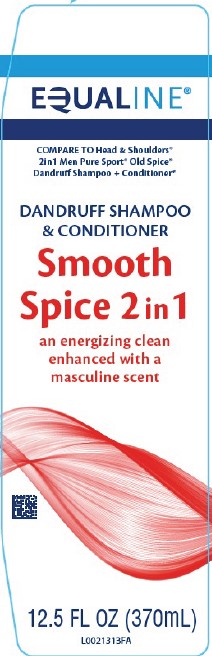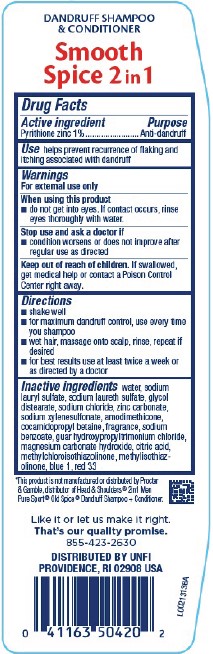 DRUG LABEL: Dandruff
NDC: 41163-253 | Form: SHAMPOO
Manufacturer: United Natural Foods, Inc. dba UNFI
Category: otc | Type: HUMAN OTC DRUG LABEL
Date: 20260217

ACTIVE INGREDIENTS: PYRITHIONE ZINC 10 mg/1 mL
INACTIVE INGREDIENTS: SODIUM LAURYL SULFATE; SODIUM LAURETH SULFATE; GLYCOL DISTEARATE; WATER; SODIUM CHLORIDE; ZINC CARBONATE; SODIUM XYLENESULFONATE; AMODIMETHICONE (800 CST); COCAMIDOPROPYL BETAINE; SODIUM BENZOATE; GUAR HYDROXYPROPYLTRIMONIUM CHLORIDE (1.7 SUBSTITUENTS PER SACCHARIDE); MAGNESIUM CARBONATE HYDROXIDE; CITRIC ACID MONOHYDRATE; METHYLCHLOROISOTHIAZOLINONE; METHYLISOTHIAZOLINONE; FD&C BLUE NO. 1; D&C RED NO. 33

Equaline 253.001/253AB-AE
Men’s Smooth Sea Scent Dandruff Shampoo & Conditioner

Claims

DANDRUFF SHAMPOO & CONDITIONER

Smooth Spice 2 in 1

Active ingredient

Pyrithione zinc 1%

Purpose

Anti-dandruff

Use

helps prevent recurrence of flaking and itching assocaited with dandruff

Warnings

For external use only

When using this product

- do not get into eyes. If contact occurs, rinse eyes thoroughly with water.

Stop use and ask a doctor if

condition worsens or does not improve after regular use as directed

Keep out of reach of children.

If swallowed, get medical help or contact a Poison Control Center right away.

Directions

- shake well
- for maximum dandruff control, use every time you shampoo
- wet hair, massage onto scalp, rinse, repeat if desired
- for best results use at least twice a week or as directed by a doctor

Inactive ingredients

water, sodium lauryl sulfate, sodium laureth sulfate, glycol distearate, sodium chloride, zinc carbonate, sodium xylenesulfonate, amodimethicone, cocamidopropyl betaine, fragrance, sodium benzoate, guar hydroxypropyltrimonium chloride, magnesium carbonate hydroxide, citric acid, methylchloroisothiazolinone, methylisothiazolinone, blue 1, red 33

Disclaimer

*This product is not manufactured or distributed by the Procter & Gamble, distributor of Head & Shoulders® 2in1 Men Pure Sport® Old Spice®

Dandruff Shampoo & Conditioner.

Adverse Reaction

Like it or let us make it right.

That's our quality promise.

855-423-2630

DISTRIBUTED BY UNFI

PROVIDENCE, RI 02908 USA

Principal display panel

EQUALINE®

COMPARE TO Head & Shoulders® 2in1 Men Pure Sport®Old Spice® Dandruff Shampoo & Conditioner*

DANDRUFF SHAMPOO & CONDITIONER

Smooth Spice 2in1

an energizing clean enhanced with a masculine scent

12.5 FL OZ (370 mL)